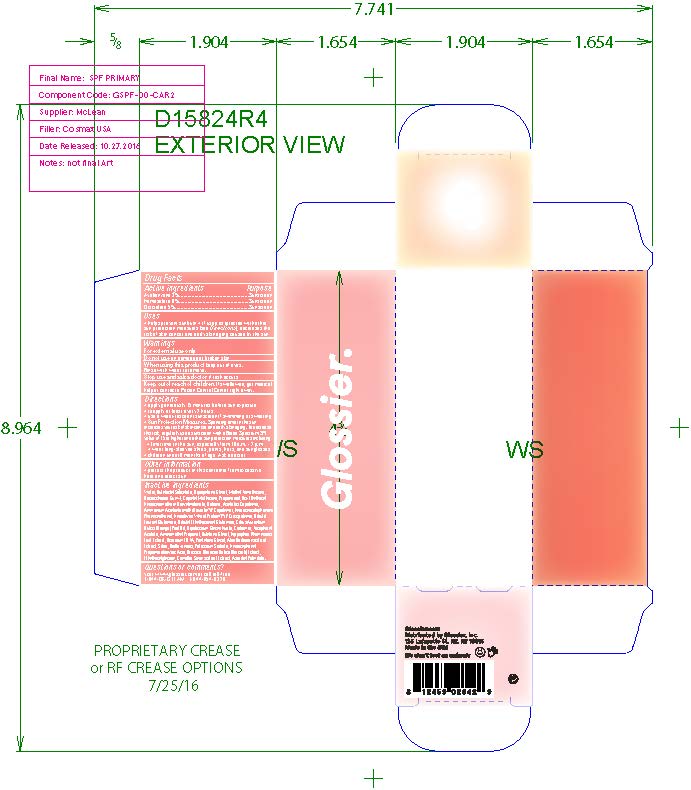 DRUG LABEL: Glossier Invisible Shield Daily Sunscreen Broad Spectrum SPF 35
NDC: 71425-010 | Form: LOTION
Manufacturer: Glossier Inc.
Category: otc | Type: HUMAN OTC DRUG LABEL
Date: 20170509

ACTIVE INGREDIENTS: AVOBENZONE 3 g/100 g; HOMOSALATE 6 g/100 g; OCTISALATE 5 g/100 g
INACTIVE INGREDIENTS: WATER; BUTYLOCTYL SALICYLATE; DIPROPYLENE GLYCOL; METHYL TRIMETHICONE; BIOSACCHARIDE GUM-4; CAPRYLYL TRIMETHICONE; PROPANEDIOL; BIS-ETHYLHEXYL HYDROXYDIMETHOXY BENZYLMALONATE; BETAINE; AMMONIUM ACRYLOYLDIMETHYLTAURATE/VP COPOLYMER; PHENOXYETHANOL; HYDROLYZED WHEAT PROTEIN (ENZYMATIC, 3000 MW); DIBUTYL LAUROYL GLUTAMIDE; CITRUS AURANTIUM FRUIT OIL; CARBOMER 940; .ALPHA.-TOCOPHEROL ACETATE; AMINOMETHYL PROPANEDIOL; BUTYLENE GLYCOL; HIPPOPHAE RHAMNOIDES FRUIT; PENTYLENE GLYCOL; CITRUS BIOFLAVONOIDS; POTASSIUM SORBATE; HYDROXYPHENYL PROPAMIDOBENZOIC ACID; BRASSICA OLERACEA VAR. BOTRYTIS WHOLE; ETHYLHEXYLGLYCERIN; CAMELLIA SINENSIS FLOWER; ASCORBYL PALMITATE

DRUG FACTS

Active Ingredients

Avobenzone 3%

Homosalate 6%

Octisalate 5%

Uses

• helps prevent sunburn • if used as directed with other
sun protection measures (see Directions), decreases the
risk of skin cancer and early skin aging caused by the sun

Warnings

For external use only
Do not use on damaged or broken skin
When using this product keep out of eyes. Rinse with water to remove.
Stop use and ask a docor if rash occurs
Keep out of reach of children. If swalled, get medical help or contact a Poison Control Center right away.

Directions

• apply generously 15 minutes before sun exposure
• reapply at least every 2 hours
• use a water-resistant sunscreen if swimming or sweating
• Sun Protection Measures. Spending time in the sun
increases your risk of skin cancer and early skin aging. To decrease
this risk, regularly use a sunscreen with a Broad Spectrum SPF
value of 15 or higher and other sun protection measures including:
• limit time in the sun, especially from 10 a.m. - 2 p.m.
• wear long-sleeved shirts, pants, hats, and sunglasses
• children under 6 months of age: Ask a doctor

Inactive ingredients

Water, Butyloctyl Salicylate, Dipropylene Glycol, Methyl Trimethicone,
Biosaccharide Gum-4, Caprylyl Methicone, Propanediol, Bis-Ethylhexyl
Hydroxydimethoxy Benzylmalonate, Betaine, Acrylates Copolymer,
Ammonium Acryloyldimethyltaurate/VP Copolymer, Hydroxyacetophenone,
Phenoxyethanol, Hydrolyzed Wheat Protein/PVP Crosspolymer, Dibutyl
Lauroyl Glutamide, Dibutyl Ethylhexanoyl Glutamide, Citrus Aurantium
Dulcis (Orange) Peel Oil, Dipotassium Glycyrrhizate, Carbomer, Tocopheryl
Acetate, Aminomethyl Propanol, Butylene Glycol, Hippophae Rhamnoides
Fruit Extract, Disodium EDTA, Pentylene Glycol, Aloe Barbadensis Leaf
Extract, Silica, Bioflavonoids, Potassium Sorbate, Hydroxyphenyl
Propamidobenzoic Acid, Brassica Oleracea Italica (Broccoli) Extract,
Ethylhexylglycerin, Camellia Sinensis Leaf Extract, Ascorbyl Palmitate.

Other Information

• protect the product in this container from excessive
heat and direct sun

Questions or Comments?

visit www.glossier.com or call toll-free
1-844-OK-GTEAM 1-844-654-8326